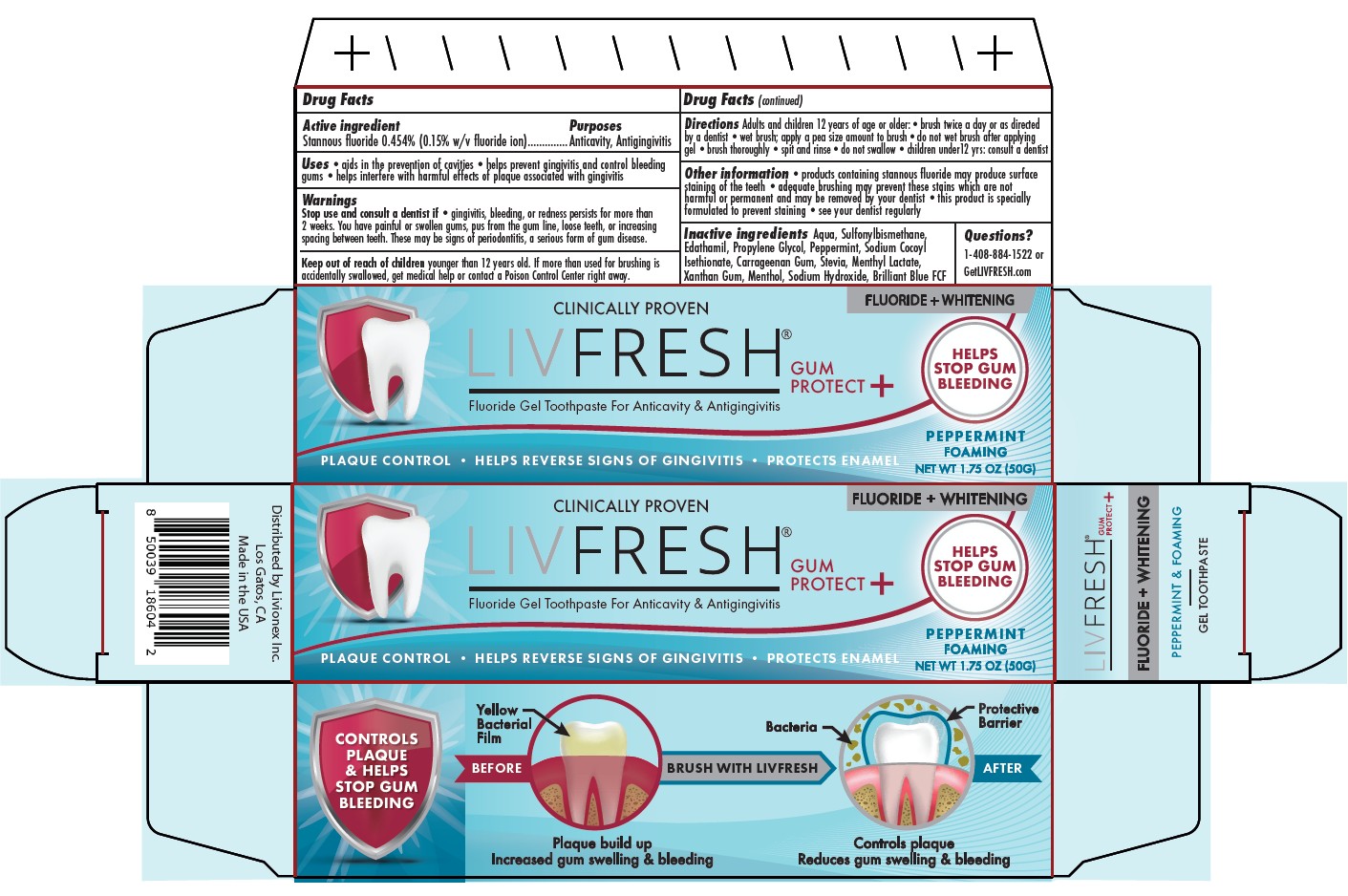 DRUG LABEL: LIVFRESH GUM PROTECT
NDC: 87398-001 | Form: GEL, DENTIFRICE
Manufacturer: Livionex Inc.
Category: otc | Type: HUMAN OTC DRUG LABEL
Date: 20260202

ACTIVE INGREDIENTS: Stannous Fluoride 4.54 mg/1 g
INACTIVE INGREDIENTS: Water; Dimethyl Sulfone; Edetate Disodium; Propylene Glycol; Sodium Cocoyl Isethionate; .Iota.-Carrageenan; Peppermint Oil; Xanthan Gum; Rebaudioside A; Menthyl Lactate, (-)-; Levomenthol; Sodium Hydroxide; Fd&C Blue No. 1

Drug Facts

Active ingredient

Stannous ﬂuoride 0.454% (0.15% w/v ﬂuoride ion)

Purposes

Anticavity, Antigingivitis

Uses

- aids in the prevention of cavities
- helps prevent gingivitis and control bleeding gums
- helps interfere with harmful effects of plaque associated with gingivitis

Stop use and consult a dentist if

- gingivitis, bleeding, or redness persists for more than 2 weeks. You have painful or swollen gums, pus from the gum line, loose teeth, or increasing spacing between teeth. These may be signs of periodontitis, a serious form of gum disease.

Keep out of reach of children

younger than 12 years old. If more than used for brushing is accidentally swallowed, get medical help or contact a Poison Control Center right away.

Directions

Adults and children 12 years of age or older:

- brush twice a day or as directed by a dentist
- wet brush; apply a pea size amount to brush
- do not wet brush after applying gel
- brush thoroughly
- spit and rinse
- do not swallow
- children under12 yrs: consult a dentist

Other information

- products containing stannous ﬂuoride may produce surface staining of the teeth
- adequate brushing may prevent these stains which are not harmful or permanent and may be removed by your dentist
- this product is specially formulated to prevent staining
- see your dentist regularly

Inactive ingredients

Aqua, Sulfonylbismethane, Edathamil, Propylene Glycol, Peppermint, Sodium Cocoyl Isethionate, Carrageenan Gum, Stevia, Menthyl Lactate, Xanthan Gum, Menthol, Sodium Hydroxide, Brilliant Blue FCF

Questions?

1-408-884-1522 or
GetLIVFRESH.com

Package Label

CLINICALLY PROVEN
LIVFRESH®
Fluoride Gel Toothpaste for Anticavity & Antigingivitis
PLAQUE CONTROL ∙ HELPS REVERSE SIGNS OF GINGIVITIS ∙ PROTECTS ENAMEL
FLUORIDE + WHITENING
GUM
PROTECT +
HELPS
STOP GUM
BLEEDING
PEPPERMINT
FOAMING
NET WT 1.74 OZ (50g)
CONTROLS
PLAQUE
& HELPS
STOP GUM
BLEEDING
BEFORE
Yellow Bacterial Film
Plaque build up
Increased gum swelling & bleeding
BRUSH WITH LIVFRESH
AFTER
Bacteria Protective Barrier
Controls plaque
Reduces gum swelling & bleeding
Distributed by Livionex Inc.
Los Gatos, CA
Made in the USA